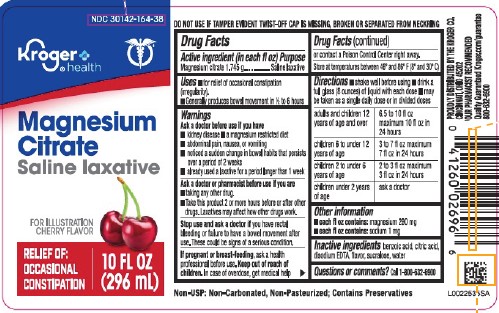 DRUG LABEL: Magnesium Citrate
NDC: 30142-164 | Form: LIQUID
Manufacturer: The Kroger Co.
Category: otc | Type: HUMAN OTC DRUG LABEL
Date: 20260227

ACTIVE INGREDIENTS: MAGNESIUM CITRATE 1.745 g/29.6 mL
INACTIVE INGREDIENTS: BENZOIC ACID; CITRIC ACID MONOHYDRATE; EDETATE DISODIUM ANHYDROUS; SUCRALOSE; WATER

Kroger 164.000/164AA R2-AB
Cherry Magnesium Citrate

Tamper Evident Statement

DO NOT USE IF TAMPER EVIDENT TWIST-OFF CAP IS MISSING, BROKEN OR SEPARATED FROM NECKRING.

Active Ingredient (in each fl oz)

Magnesium citrate 1.745 g

Purpose

Saline laxative

Uses

- for relief of occasional constipation (irregularity).
- Generally produces bowel movement in 1/2 to 6 hours

Warnings

for this product

Ask a doctor before use if you have

- kidney disease
- a magnesium restricted diet
- abdominal pain, nausea, or vomiting
- noticed a sudden change in bowel habits that persists over a period of 2 weeks
- already used a laxative for a period longer than 1 week

Ask a doctor or pharmacist before use if you are

- taking any other drug.
- Take this product 2 or more hours before or after other drugs. Laxatives may affect how other drugs work.

Stop use and ask a doctor if

you have rectal bleeding or failure to have a bowel movement after use. These could be signs of a serious condition.

If pregnant or breast-feeding,

ask health professional before use.

Keep out of reach of children.

In case of overdose, get medical help or contact a Poison Control Center right away.

Storage

Store at temperatures betweem 46° and 86°F (8° and 30° C)

Directions

- shake well before using
- drink a full glass (8 ounces) of liquid with each dose
- may be taken as a single daily dose or in divided doses

adults and children 12 years of age and over - 6.5 to 10 fl oz maximum 10 fl oz in 24 hours

children 6 to under 12 years of age - 3 to 7 fl oz maximum 7 fl oz in 24 hours

children 2 to under 6 years of age - 2 to 3 fl oz maximum 3 fl oz in 24 hours

children under 2 years of age - ask a doctor

other information

- each fl oz contains: magnesium 290 mg
- each fl oz contains: sodium 1 mg

Inactive ingredients

benzoic acid, citric acid, disodium EDTA, flavor, sucralose, water

Questions or comments?

Call 1-800-632-6900

Claims

Non-USP: Non-Carbonated, Non-Pasteurized; Contains Preservatives

ADVERSE REACTIONS SECTION

PROUDLY DISTRIBUTED BY THE KROGER CO.

CINCINNATI, OHIO 45202

‡Our Pharmacist Recommended

QUALITY GUARANTEED www.kroger.com/guarantee

800-632-6900

principal display panel

NDC 30142-164-38

Kroger® health

Magnesium Citrate

SALINE LAXATIVE

For Illustration Cherry Flavor

RELIEF OF: OCCASIONAL CONSTIPATION

10 FL OZ (296 mL)